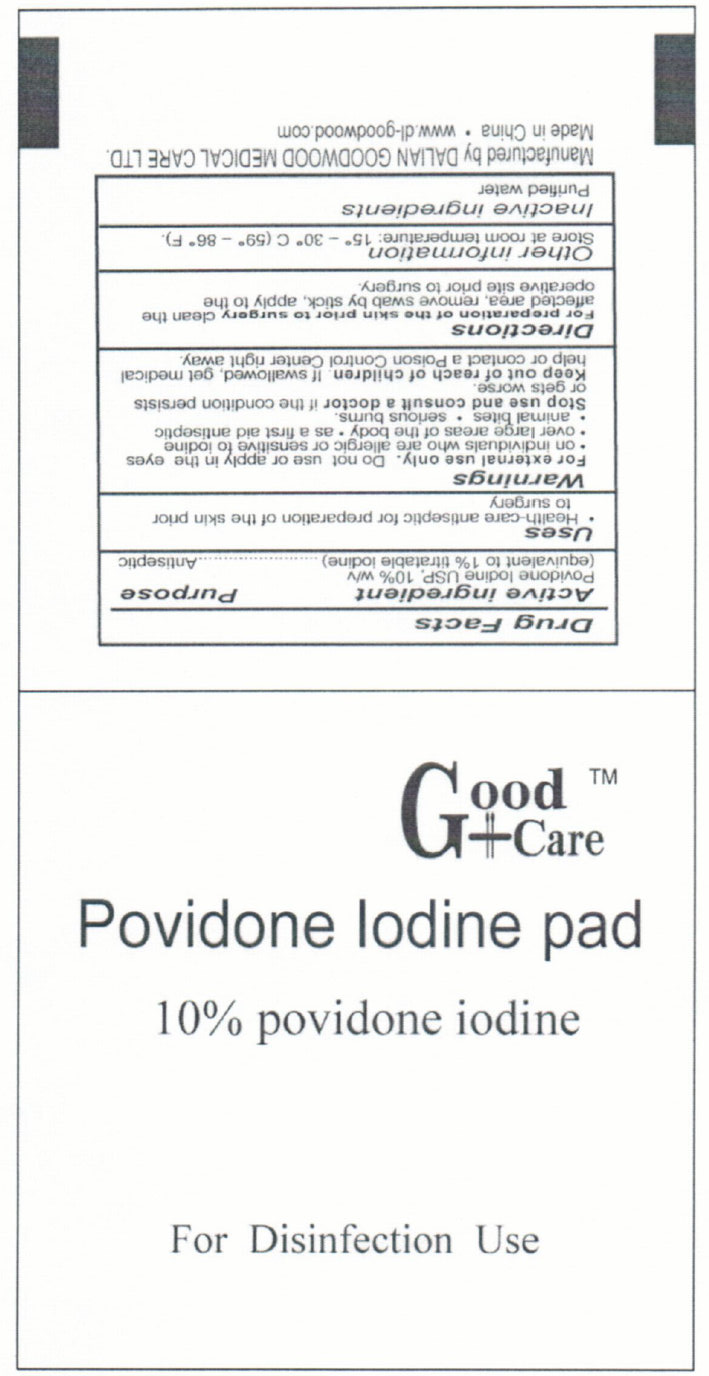 DRUG LABEL: Good Care Povidone Iodine Pad
NDC: 50685-007 | Form: SWAB
Manufacturer: Dalian Goodwood Medical Care Ltd.
Category: otc | Type: HUMAN OTC DRUG LABEL
Date: 20230525

ACTIVE INGREDIENTS: POVIDONE-IODINE 10 mg/1 mL
INACTIVE INGREDIENTS: WATER

Good Care Povidone Iodine Pad 10% Povidone Iodine

Active Ingredient

Povidone Iodine USP, 10% w/v

(equivalent to 1% titratable iodine)

Purpose

Antiseptic

Uses

- Health-care antiseptic for preparation of the skin prior to surgery

Warnings

For external use only.

Do not use or apply in the eyes on individuals who are allergic or sensitive to iodine
over large areas of the body
as a first aid antiseptic
animal bites
serious burns

Stop use and consult a doctor if the condition persists or gets worse.

Keep out of reach of children. If swallowed, get medical help or contact a Poison Control Center right away.

Directions

For preparation of the skin prior to surgery clean the affected area, remove swab by the stick, apply to the operative site prior to surgery.

Other information

Store at room temperature: 15 degrees - 30 degrees C (59 degrees - 86 degrees F)

Inactive ingredients

Purified water

Manufactured by DALIAN GOODWOOD MEDICAL CARE LTD.

Made in China www.dl-goodwood.com

PACKAGE LABEL

Good Care

Povidone Iodine pad
10% povidone iodine

For Disinfection Use